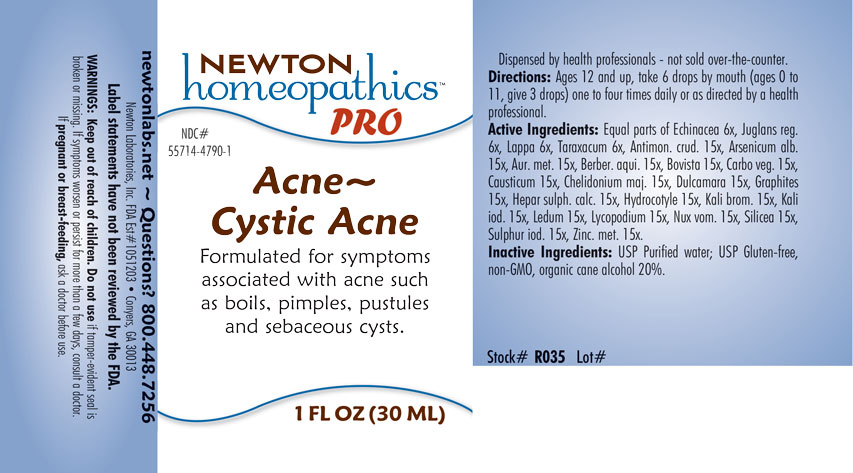 DRUG LABEL: Acne - Cystic Acne
NDC: 55714-4790 | Form: LIQUID
Manufacturer: Newton Laboratories, Inc
Category: homeopathic | Type: HUMAN OTC DRUG LABEL
Date: 20201202

ACTIVE INGREDIENTS: CAUSTICUM 15 [hp_X]/1 mL; CHELIDONIUM MAJUS 15 [hp_X]/1 mL; SOLANUM DULCAMARA WHOLE 15 [hp_X]/1 mL; CALCIUM SULFIDE 15 [hp_X]/1 mL; CENTELLA ASIATICA 15 [hp_X]/1 mL; ECHINACEA, UNSPECIFIED 6 [hp_X]/1 mL; JUGLANS REGIA WHOLE 6 [hp_X]/1 mL; GOLD 15 [hp_X]/1 mL; TARAXACUM OFFICINALE 6 [hp_X]/1 mL; ANTIMONY TRISULFIDE 15 [hp_X]/1 mL; BERBERIS AQUIFOLIUM WHOLE 15 [hp_X]/1 mL; CALVATIA GIGANTEA WHOLE 15 [hp_X]/1 mL; POTASSIUM BROMIDE 15 [hp_X]/1 mL; ARCTIUM LAPPA WHOLE 6 [hp_X]/1 mL; ARSENIC TRIOXIDE 15 [hp_X]/1 mL; ACTIVATED CHARCOAL 15 [hp_X]/1 mL; GRAPHITE 15 [hp_X]/1 mL; ZINC 15 [hp_X]/1 mL; POTASSIUM IODIDE 15 [hp_X]/1 mL; LEDUM PALUSTRE WHOLE 15 [hp_X]/1 mL; SILICON DIOXIDE 15 [hp_X]/1 mL; SULFUR IODIDE 15 [hp_X]/1 mL; LYCOPODIUM CLAVATUM WHOLE 15 [hp_X]/1 mL; STRYCHNOS NUX-VOMICA WHOLE 15 [hp_X]/1 mL
INACTIVE INGREDIENTS: WATER; ALCOHOL

Acne 4790L

INDICATIONS & USAGE SECTION

Formulated for symptoms associated with acne such as boils, pimples, pustules, and sebaceous cysts.

DOSAGE & ADMINISTRATION SECTION

Directions: Ages 12 and up, take 6 drops by mouth (ages 0 to 11, give 3 drops) one to four times a day or as directed by a health professional.

OTC - ACTIVE INGREDIENT SECTION

Equal parts of Echinacea 6x, Juglans reg. 6x, Lappa 6x, Taraxacum 6x, Antimon. crud. 15x, Arsenicum alb. 15x, Aur. met. 15x, Berber. aqui. 15x, Bovista 15x, Carbo veg. 15x, Causticum 15x, Chelidonium maj. 15x, Dulcamara 15x, Graphites 15x, Hepar sulph. calc. 15x, Hydrocotyle 15x, Kali brom. 15x, Kali iod. 15x, Ledum 15x, Lycopodium 15x, Nux vom. 15x, Silicea 15x, Sulphur iod. 15x, Zinc. met. 15x.

OTC - PURPOSE SECTION

Formulated for symptoms associated with acne such as boils, pimples, pustules and sebaceous cysts.

INACTIVE INGREDIENT SECTION

USP Purified water; USP Gluten-free, non-GMO, organic cane alcohol 20%.

QUESTIONS SECTION

newtonlabs.net - Questions? 800.448.7256

Newton Laboratories, Inc. FDA Est # 1051203 - Conyers, GA 30013

WARNINGS SECTION

WARNINGS: Keep out of reach of children. Do not use if tamper-evident seal is broken or missing. If symptoms worsen or persist for more than a few days, consult a doctor. If pregnant or breast-feeding, ask a doctor before use.

OTC - PREGNANCY OR BREAST FEEDING SECTION

If pregnant or breast-feeding, ask a doctor before use.

OTC - KEEP OUT OF REACH OF CHILDREN SECTION

Keep out of reach of children.